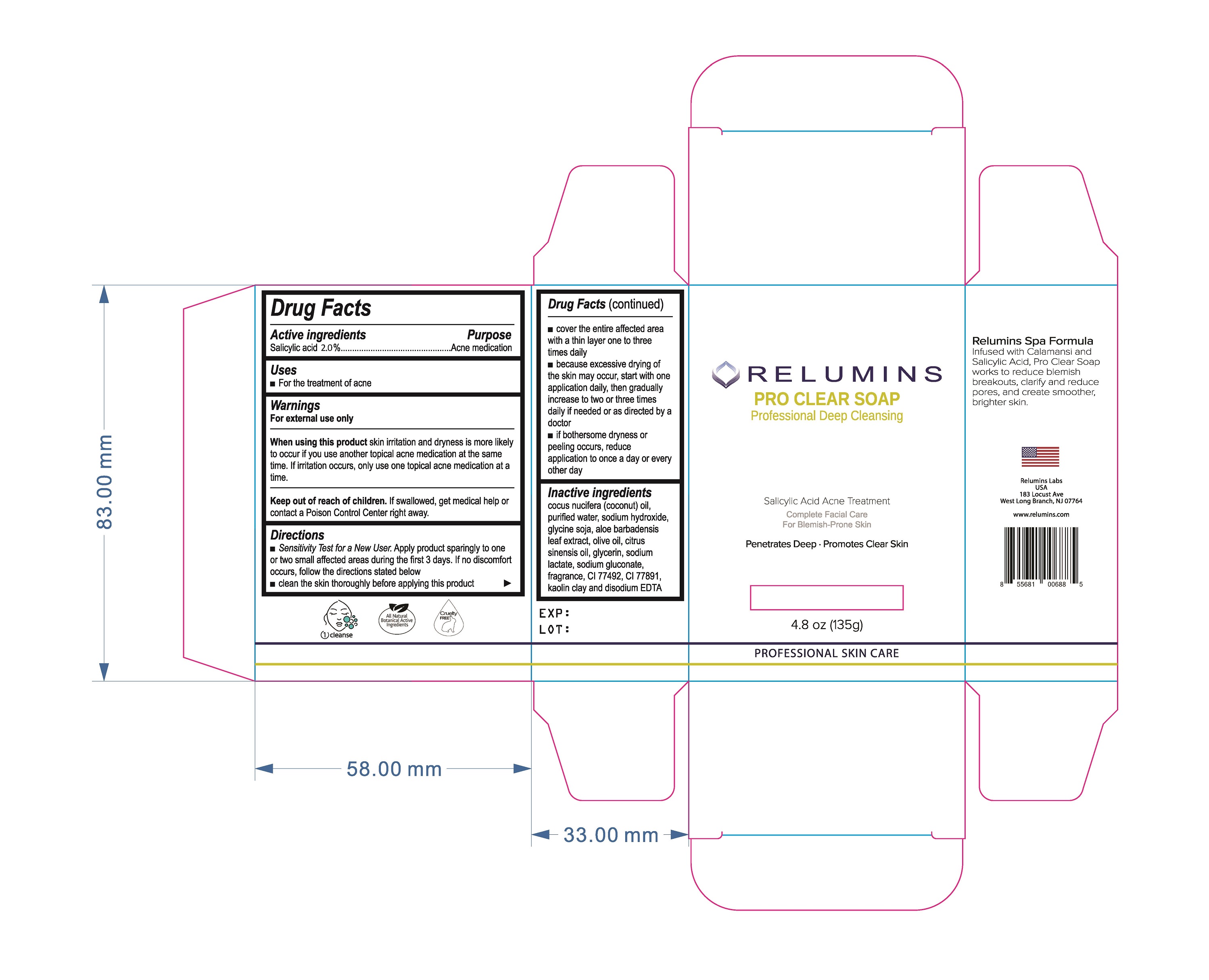 DRUG LABEL: AcneFree Dermatology Inspired Care Blackhead Removing Scrub Acne Treatment
NDC: 79061-259 | Form: GEL
Manufacturer: Relumins Labs LLC
Category: otc | Type: HUMAN OTC DRUG LABEL
Date: 20210701

ACTIVE INGREDIENTS: SALICYLIC ACID 2 mg/100 mL
INACTIVE INGREDIENTS: COCONUT OIL; WATER; SODIUM HYDROXIDE; SOYBEAN; ALOE VERA LEAF; OLIVE OIL; CITRUS SINENSIS FLOWER OIL; GLYCERIN; SODIUM LACTATE; SODIUM GLUCONATE; FRAGRANCE CLEAN ORC0600327; FERRIC OXIDE YELLOW; TITANIUM DIOXIDE; KAOLIN; DISODIUM EDTA-COPPER

Relumins Pro Clear Soap: Professional Deep Cleaning

Active ingredient

Salicylic acid 2%

Uses

For the treatment of acne

Warnings

For external use only

When using this product

- skin irritation and dryness is more likely to occur if you use another topical acne medication at the same time. If irritation occurs, only use one topical acne medication at a time.

Keep out of reach of children.

If swallowed, get medical help or contact a Poison Control Center right away.

Inactive ingredients

cocus nucifera (coconut) oil, purified water, sodium hydroxide, glycine soja, aloe barbadensis leaf extract, olive oil, citrus sinesis oil, glycerin, sodium lactate, sodium glucconate, fragrance, CI 77492, CI 77891, kaolin clay and disodium EDTA